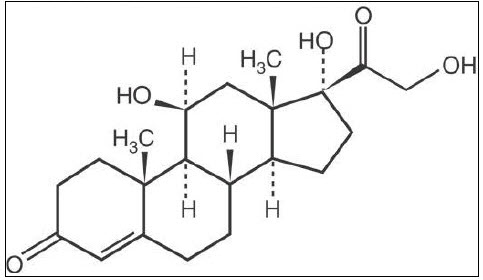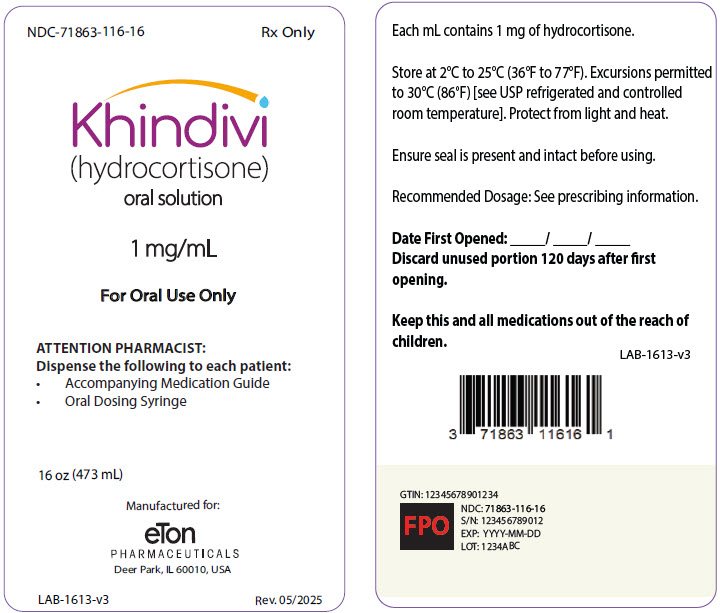 DRUG LABEL: Khindivi
NDC: 71863-116 | Form: SOLUTION
Manufacturer: Eton Pharmaceuticals, Inc.
Category: prescription | Type: HUMAN PRESCRIPTION DRUG LABEL
Date: 20250730

ACTIVE INGREDIENTS: HYDROCORTISONE 1 mg/1 mL
INACTIVE INGREDIENTS: POLYETHYLENE GLYCOL, UNSPECIFIED; PROPYLENE GLYCOL; METHYLPARABEN; PROPYLPARABEN; SUCRALOSE; ETHYL MALTOL; BUTYLATED HYDROXYANISOLE; GLYCERIN

HIGHLIGHTS OF PRESCRIBING INFORMATION

These highlights do not include all the information needed to use KHINDIVI™ safely and effectively. See full prescribing information for KHINDIVI™.
KHINDIVI™ (hydrocortisone) oral solution
Initial U.S. Approval: 1952

1 INDICATIONS AND USAGE

KHINDIVI is a corticosteroid indicated as replacement therapy in pediatric patients 5 years of age and older with adrenocortical insufficiency. (1)

Limitations of Use

KHINDIVI is not approved for increased dosing during periods of stress or acute events. Use a different hydrocortisone-containing drug product for stress dosing [see Warnings and Precautions (5.1)] .

2 DOSAGE AND ADMINISTRATION

- Individualize the dose, using the lowest possible dosage. (2.1)
- When stress dosing is needed use a different hydrocortisone containing drug product. (2.1)
- The recommended starting replacement dosage of KHINDIVI is 8 to 10 mg/m^2daily. Higher doses may be needed based on the patient's age and symptoms of the disease. Use of lower starting doses may be sufficient in patients with residual but decreased endogenous cortisol production. (2.2)
- Divide the total daily dose into 3 doses and administer 3 times daily. Older patients may have their daily dose divided by 2 and administered twice daily. (2.2)
- KHINDIVI contains the inactive ingredients polyethylene glycol 400, propylene glycol, and glycerin. If patients experience adverse reactions (i.e., hyperosmolarity, metabolic acidosis, hypoglycemia, hepato-renal injury, central nervous system toxicity, and gastrointestinal adverse reactions), consider discontinuation of KHINDIVI and switch to another hydrocortisone product. (2.3)
- When switching from other oral hydrocortisone formulations, use the same total daily hydrocortisone dosage. If symptoms of adrenal insufficiency occur, increase total daily dosage. (2.4)
- See the Full Prescribing Information for detailed dosing and administration instructions. (2)

3 DOSAGE FORMS AND STRENGTHS

- Oral solution: 1 mg/mL. (3)

4 CONTRAINDICATIONS

- Hypersensitivity to hydrocortisone or any component of KHINDIVI. (4)

5 WARNINGS AND PRECAUTIONS

- Adrenal Crisis: Undertreatment, sudden discontinuation of therapy, or switching from another oral hydrocortisone formulation may lead to adrenocortical insufficiency, adrenal crisis and death. Adrenal crisis may also be induced by stress events such as infections or surgery. During periods of stress switch to another oral hydrocortisone product and increase the dose. Switch patients who are vomiting, severely ill or unable to take oral medications to parenteral corticosteroid formulations. (5.1)
- Systemic Adverse Reactions Due to Inactive Ingredients: KHINDIVI contains the inactive ingredients polyethylene glycol 400, propylene and glycol, and glycerin, which may cause hyperosmolarity, metabolic acidosis, hypoglycemia, hepato-renal injury, central nervous toxicity, gastrointestinal adverse reactions. Discontinue KHINDIVI and switch to another hydrocortisone product if these adverse reactions occur. (5.2)
- Immunosuppression and Increased Risk of Infection with Use of a Dosage Greater Than Replacement: Use of a greater than replacement dosage can suppress the immune system and increase the risks of new infections or exacerbation of latent infections with any pathogen, including viral, bacterial, fungal, protozoan, or helminthic infections. Monitor patients for signs and symptoms of infections. (5.3)
- Growth Retardation: Long-term use in excessive doses may cause growth retardation. Use the minimum dosage of KHINDIVI to achieve desired clinical response and monitor the patient's growth. (5.4)
- Cushing's Syndrome Due to Use of Excessive Doses of Corticosteroids:Prolonged use with supraphysiologic doses may cause Cushing's syndrome. Monitor patients for signs and symptoms of Cushing's syndrome every 6 months. (5.5)
- Decrease in Bone Mineral Density: Corticosteroids decrease bone formation and increase bone resorption which may lead to inhibition of bone growth and development of osteoporosis. Use the minimum dosage of KHINDIVI to achieve desired clinical response.(5.6)
- Psychiatric Adverse Reactions: Use may be associated with severe psychiatric adverse reactions such as euphoria, mania, psychosis with hallucinations and delirium or depression. Symptoms typically emerge within a few days or weeks of starting the treatment. Most reactions resolve after either dose reduction or withdrawal, although specific treatment may be necessary. Monitor patients for behavioral and mood disturbances during treatment. Instruct caregivers and/or patients to seek medical advice if psychiatric symptoms develop. (5.7)
- Ophthalmic Adverse Reactions: Cataracts, glaucoma and central serous chorioretinopathy have been reported with prolonged use of high doses. Monitor patients for blurred vision or other visual disturbances and if they occur, refer them to an ophthalmologist. (5.8)
- Gastrointestinal Adverse Reactions: Increased risk in patients with certain gastrointestinal disorders. Signs and symptoms may be masked. (5.9)

6 ADVERSE REACTIONS

Common adverse reactions for corticosteroids include fluid retention, alteration in glucose tolerance, elevation in blood pressure, behavioral and mood changes, increased appetite, and weight gain. (6)

To report SUSPECTED ADVERSE REACTIONS, contact Eton Pharmaceuticals, Inc. at 1-855-224-0233 or FDA at 1-800-FDA-1088 or www.fda.gov/medwatch.

7 DRUG INTERACTIONS

- CYP3A4 Inhibitors: concomitant administration may require a decrease in the KHINDIVI dose. (7)
- CYP3A4 Inducers: concomitant administration may require an increase in the KHINDIVI dose. (7)
- Estrogen and Estrogen-Containing Products: concomitant administration may require an increase in the KHINDIVI dose. (7)
- Antidiabetic agents: excessive doses may increase blood glucose concentrations. Dose adjustment of antidiabetic agents may be required. (7)
- NSAIDs: concomitant administration increases risk of gastrointestinal adverse reactions. (7)

FULL PRESCRIBING INFORMATION

1 INDICATIONS AND USAGE

KHINDIVI is indicated as replacement therapy in pediatric patients 5 years of age and older with adrenocortical insufficiency.

Limitations of Use

KHINDIVI is not approved for increased dosing during periods of stress or acute events. Use a different hydrocortisone-containing drug product for stress dosing [(see Warnings and Precautions (5.1)] .

2 DOSAGE AND ADMINISTRATION

2.1 Important Considerations for Dosing

- Individualize the dose for each patient, using the lowest possible dosage.
- Monitor patients for symptoms of under and/or overtreatment including signs and symptoms of adrenocortical insufficiency, linear growth, and weight gain. Adjust doses accordingly.
- When stress dosing is needed (during episodes of acute febrile illness, gastroenteritis, surgery or major trauma) use a different hydrocortisone-containing drug product. [see Warnings and Precautions (5.1)] .

2.2 Recommended Dosage and Administration

- The recommended starting replacement dosage of KHINDIVI is 8 to 10 mg/m^2daily administered orally with or without food. Higher doses may be needed based on the patient's age and symptoms of the disease. Use of lower starting dose may be sufficient in patients with residual but decreased endogenous cortisol production.
- Round the dose to the nearest 0.5 mg or 1 mg.
- Divide the total daily dose into 3 doses and administer 3 times daily. Older pediatric patients may have their daily dose divided by 2 and administered twice daily.
- Administer KHINDIVI using the oral syringe provided by the pharmacy.
- KHINDIVI may be administered through a gastric tube. Flush gastric tube with 20 mL of water to ensure the entire dose is delivered.

2.3 Discontinue KHINDIVI Due to Adverse Reactions Associated with Inactive Ingredients

- KHINDIVI contains the inactive ingredients polyethylene glycol 400, propylene glycol, and glycerin, which have been associated with hyperosmolarity, metabolic acidosis, hypoglycemia, hepato-renal injury, central nervous system toxicity, and gastrointestinal adverse reactions. If patient presents with adverse reactions that could be related to these conditions, monitor the patient, and consider discontinuation of KHINDIVI and switching to another hydrocortisone product [see Warnings and Precautions (5.2)] .

2.4 Switching to KHINDIVI from Other Oral Hydrocortisone Formulations

- When switching patients to KHINDIVI from other oral hydrocortisone formulations to KHINDIVI use the same total daily hydrocortisone dosage. After switching to KHINDIVI, monitor patients for symptoms of adrenocortical insufficiency. If symptoms of adrenal insufficiency occur after switching, increase the total daily dosage of KHINDIVI [see Dosage and Administration (2.2)and Warnings and Precautions (5.1, 5.2)].

3 DOSAGE FORMS AND STRENGTHS

KHINDIVI oral solution, 1 mg/mL is a clear, colorless to slightly yellow colored viscous oral solution.

4 CONTRAINDICATIONS

KHINDIVI is contraindicated in patients with hypersensitivity to hydrocortisone or to any component of KHINDIVI. Reactions have included anaphylaxis in patients receiving corticosteroids [see Adverse Reactions (6.2)] .

5 WARNINGS AND PRECAUTIONS

5.1 Adrenal Crisis

Undertreatment with KHINDIVI or sudden discontinuation of therapy with KHINDIVI may lead to adrenocortical insufficiency, adrenal crisis, and death. Adrenal crisis may also be induced by stress events such as infections or surgery when patients require higher doses of corticosteroids. Symptoms of adrenocortical insufficiency include poor feeding, fatigue, low muscle tone, joint pain, nausea, vomiting, hypoglycemia, low blood pressure and electrolyte disturbances.

During periods of stress (e.g., infections, surgery), switch to another oral hydrocortisone product and increase the dose, if oral medications are tolerated. Switch patients who are vomiting, severely ill, or unable to take oral medications to parenteral corticosteroid formulations without delay. Once the patient recovers, gradually reduce the steroid dosage used during the acute event and do not switch back to KHINDIVI until the maintenance dosage can be resumed.

KHINDIVI is not approved for stress dosing. KHINDIVI contains inactive ingredients polyethylene glycol 400, propylene glycol, and glycerin at levels that individually or in combination may result in hyperosmolarity, metabolic acidosis, hypoglycemia, hepato-renal injury, central nervous system toxicity (e.g., seizure and coma) and/or gastrointestinal adverse reactions [see Warnings and Precautions (5.2)] . Use of KHINDIVI for stress dosing will result in a greater exposure to inactive ingredients and may increase the risk of these adverse reactions.

When switching patients to KHINDIVI from other oral hydrocortisone formulations, consider the potential for dosing inaccuracy if other oral hydrocortisone formulations have been manipulated (e.g., split or crushed tablets, compounded formulations). Manipulation of oral hydrocortisone formulations may result in a relative difference in hydrocortisone exposure when using the same dosage to initiate KHINDIVI treatment. Monitor patients after switching to KHINDIVI to ensure KHINDIVI is providing the same level of hydrocortisone exposure as the previously used oral hydrocortisone formulation. If symptoms of adrenal insufficiency occur, increase the total daily dosage of KHINDIVI.

5.2 Systemic Adverse Reactions Due to Inactive Ingredients

Hyperosmolarity

KHINDIVI is not approved in pediatric patients less than 5 years of age. KHINDIVI contains the inactive ingredients polyethylene glycol 400, propylene glycol, and glycerin, which undergo substantial systemic absorption. These inactive ingredients, individually or in combination may increase plasma osmolarity in all pediatric patients, especially in pediatric patients less than 5 years of age due to incomplete maturity of the alcohol dehydrogenase enzyme that metabolizes propylene glycol and polyethylene glycol 400.

Monitor pediatric patients using KHINDIVI for signs and symptoms consistent with hyperosmolarity. Discontinue KHINDIVI and switch to another hydrocortisone formulation if this occurs.

Metabolic Acidosis and Other Adverse Reactions

KHINDIVI contains the inactive ingredient polyethylene glycol 400 and propylene glycol that may result in metabolic acidosis, hypoglycemia, hepato-renal injury, and central nervous system toxicity (e.g., seizure and coma). These adverse reactions may increase the risk of adrenal crisis [see Warnings and Precautions (5.1)] . Monitor laboratory values and for physical signs and symptoms of these adverse reactions. Discontinue KHINDIVI and switch to another hydrocortisone formulation if these adverse reactions occur.

Laxative Effects Due to Inactive Ingredients

KHINDIVI contains the inactive ingredients polyethylene glycol 400 and glycerin, which alone or in combination, may cause gastrointestinal irritation resulting in vomiting and/or diarrhea. These gastrointestinal reactions may increase the risk of adrenal crisis in patients with adrenal insufficiency [see Warnings and Precautions (5.1)] . Monitor for signs or symptoms of gastrointestinal irritation and associated fluid and electrolyte abnormalities. Discontinue KHINDIVI and switch to another hydrocortisone formulation if these adverse reactions occur.

5.3 Immunosuppression and Increased Risk of Infection with Use of a Dosage Greater Than Replacement

Use of the recommended dosage of KHINDIVI [see Dosage and Administration (2.1, 2.2)] as a replacement therapy in pediatric patients with adrenocortical insufficiency is not expected to cause immunosuppression or increase the risk of infection. The use of a greater than replacement dosage can suppress the immune system and increase the risk of infection with any pathogen, including viral, bacterial, fungal, protozoan, or helminthic pathogens. The use of KHINDIVI at greater than replacement dosage can:

- Reduce resistance to new infections
- Exacerbate existing infections
- Increase the risk of disseminated infections
- Increase the risk of reactivation or exacerbation of latent infections
- Mask some signs of infection

Infections associated with the use of corticosteroids at a greater than replacement dosage range from mild to severe or fatal, and the rate of infectious complications increases with increasing corticosteroid dosages.

Monitor for the development of infection and consider KHINDIVI dosage reduction as needed [see Warnings and Precautions (5.1)].

5.4 Growth Retardation

Long-term use of corticosteroids in excessive doses may cause growth retardation in pediatric patients. Historical cohorts of adults treated from childhood for congenital adrenal hyperplasia have been found to have growth retardation. Effects on linear growth are less likely when using corticosteroids as replacement therapy. Use the minimum dosage of KHINDIVI to achieve desired clinical response and monitor the patient's growth.

5.5 Cushing's Syndrome Due to Use of Excessive Doses of Corticosteroids

Prolonged use of corticosteroids in supraphysiologic doses may cause Cushing's syndrome. Symptoms and signs of Cushing's syndrome include weight gain, decreased height velocity, hyperglycemia, hypertension, edema, easy bruising, muscle weakness, red round face, depression, or mood swings. Monitor patients for signs and symptoms of Cushing's syndrome every 6 months.

5.6 Decrease in Bone Mineral Density

Corticosteroids decrease bone formation and increase bone resorption which may lead to development of osteoporosis. Historical cohorts of adults treated from childhood for congenital adrenal hyperplasia have been found to have reduced bone mineral density and increased fracture rates. Use the minimum dosage of KHINDIVI to achieve desired clinical response.

5.7 Psychiatric Adverse Reactions

Corticosteroid use may be associated with severe psychiatric adverse reactions. Euphoria, mania, psychosis with hallucinations and delirium or depression have been seen in patients at replacement doses of hydrocortisone [see Adverse Reactions (6)]. Symptoms typically emerge within a few days or weeks of starting the treatment. Risks may be higher with high doses, although dose levels do not allow prediction of the onset, type, severity, or duration of reactions. Most reactions resolve after either dose reduction or withdrawal, although specific treatment may be necessary. Monitor patients for behavioral and mood disturbances during treatment with KHINDIVI. Instruct caregivers and/or patients to seek medical advice if psychiatric symptoms develop.

5.8 Ophthalmic Adverse Reactions

Ophthalmic effects, such as cataract, glaucoma or central serous chorioretinopathy have been reported with prolonged use of corticosteroids in high doses. Monitor patients for blurred vision or other visual disturbances. If patients develop ophthalmic adverse reactions, refer them to an ophthalmologist for further evaluation.

5.9 Gastrointestinal Adverse Reactions

Gastrointestinal Perforation

There is an increased risk of gastrointestinal perforation in patients with certain gastrointestinal disorders. Signs of gastrointestinal perforation, such as peritoneal irritation may be masked in patients receiving corticosteroids. Corticosteroids should be used with caution if there is a probability of impending perforation, abscess, or other pyogenic infections, diverticulitis, fresh intestinal anastomoses, and active or latent peptic ulcer.

Concomitant Use with Non-Steroidal Anti-Inflammatory Drugs

Concurrent administration of corticosteroids with non-steroidal anti-inflammatory drugs (NSAIDS) may increase the risk of gastrointestinal adverse reactions. Monitor patients receiving corticosteroids and concomitant NSAIDS for gastrointestinal adverse reactions [see Drug Interactions (7)].

5.10 Risk of Kaposi's Sarcoma with Use of a Dosage Greater Than Replacement

Kaposi's sarcoma has been reported to occur in patients receiving corticosteroid therapy, most often for chronic conditions at a dosage greater than replacement (supraphysiologic dosage). If patients take a supraphysiologic chronic dosage of KHINDIVI, they are at increased risk of developing Kaposi's sarcoma.

5.11 Vaccination

Administration of live vaccines may be acceptable in KHINDIVI-treated pediatric patients with adrenocortical insufficiency who receive replacement corticosteroids.

6 ADVERSE REACTIONS

The following serious adverse reactions are described here and elsewhere in the label:

- Adrenal Crisis [see Warnings and Precautions (5.1)]
- Systemic Adverse Reactions Due to Inactive Ingredients [see Warnings and Precautions (5.2)]
- Immunosuppression and Increased Risk of Infection with Use of a Dosage Greater Than Replacement [see Warnings and Precautions (5.3)]
- Growth Retardation [see Warnings and Precautions (5.4)]
- Cushing's Syndrome Due to Use of Excessive Doses of Corticosteroids [see Warnings and Precautions (5.5)]
- Decrease in Bone Mineral Density [see Warnings and Precautions (5.6)]
- Psychiatric Adverse Reactions [see Warnings and Precautions (5.7)]
- Ophthalmic Adverse Reactions [see Warnings and Precautions (5.8)]
- Gastrointestinal Adverse Reactions [see Warnings and Precautions (5.9)]
- Risk of Kaposi's Sarcoma with Use of Dosage Greater than Replacement [see Warnings and Precautions (5.10)]
- Vaccinations [see Warnings and Precautions (5.11)]

6.1 Clinical Trials Experience

Because clinical studies are conducted under widely varying conditions, adverse reaction rates observed in the clinical trials of a drug cannot be directly compared to rates in the clinical trials of another drug and may not reflect the rates observed in practice.

The safety of oral hydrocortisone was evaluated in an uncontrolled, open-label, single-arm clinical study in 18 pediatric patients with adrenocortical insufficiency treated with oral hydrocortisone granules. Adrenocortical insufficiency was due to congenital adrenal hyperplasia in 17 patients and to hypopituitarism in one patient. All patients received at least one dose of hydrocortisone granules. The age ranged from 36 days to 5.7 years at start of treatment; 8 patients were female and 10 were male; 100% were White. Adverse reactions that were reported in two or more patients (≥ 11%) are shown in Table 1.

Table 1: Adverse Reactions Occurring in ≥11% of Pediatric Patients with Adrenocortical Insufficiency Treated with Hydrocortisone Granules for up to 29 Months
Adverse Reactions | N=18 n (%)
Pyrexia | 10 (56)
Gastroenteritis | 9 (50)
Viral upper respiratory tract infection | 8 (44)
Vomiting | 7 (39)
Viral infection | 6 (33)
Conjunctivitis | 5 (28)
Otitis media viral | 3 (17)
Tonsillitis | 3 (17)
Body temperature increased | 2 (11)
Bronchitis | 2 (11)
Dental caries | 2 (11)
Diarrhea | 2 (11)
Genitourinary operation | 2 (11)
Pharyngitis | 2 (11)
Respiratory tract infection | 2 (11)
Rhinitis | 2 (11)

6.2 Postmarketing Experience

The following adverse reactions seen in pediatric and adult patients associated with the use of corticosteroids were identified in the literature and from postmarketing reports. Because some of these reactions are reported voluntarily from a population of uncertain size, it is not always possible to reliably estimate their frequency or establish a causal relationship to drug exposure.

Common adverse reactions for corticosteroids include fluid retention, alteration in glucose tolerance, elevation in blood pressure, behavioral and mood changes, increased appetite and weight gain.

Allergic Reactions:Anaphylaxis, angioedema

Cardiovascular:Bradycardia, cardiac arrest, cardiac arrhythmias, cardiac enlargement, circulatory collapse, congestive heart failure, fat embolism, hypertension, hypertrophic cardiomyopathy in premature infants, myocardial rupture following recent myocardial infarction, pulmonary edema, syncope, tachycardia, thromboembolism, thrombophlebitis, vasculitis

Dermatologic:Acne, allergic dermatitis, cutaneous and subcutaneous atrophy, dry scalp, edema, facial erythema, hyper or hypo-pigmentation, impaired wound healing, increased sweating, petechiae and ecchymoses, rash, sterile abscess, striae, suppressed reactions to skin tests, thin fragile skin, thinning scalp hair, urticaria

Endocrine:Abnormal fat deposits, decreased carbohydrate tolerance, development of Cushingoid state, hirsutism, manifestations of latent diabetes mellitus and increased requirements for insulin or oral hypoglycemic agents in diabetics, menstrual irregularities, moon faces, secondary adrenocortical and pituitary unresponsiveness (particularly in times of stress, as in trauma, surgery or illness), suppression of growth in pediatric patients

Fluid and Electrolyte Disturbances:Fluid retention, potassium loss, hypertension, hypokalemic alkalosis, sodium retention

Gastrointestinal:Abdominal distention, elevation in serum liver enzymes levels (usually reversible upon discontinuation), hepatomegaly, hiccups, malaise, nausea, pancreatitis, peptic ulcer with possible perforation and hemorrhage, ulcerative esophagitis

General:Increased appetite and weight gain

Metabolic:Negative nitrogen balance due to protein catabolism

Musculoskeletal:Osteonecrosis of femoral and humeral heads, Charcot-like arthropathy, loss of muscle mass, muscle weakness, osteoporosis, pathologic fracture of long bones, steroid myopathy, tendon rupture, vertebral compression fractures

Neurological:Arachnoiditis, convulsions, depression, emotional instability, euphoria, headache, increased intracranial pressure with papilledema (pseudo-tumor cerebri) usually following discontinuation of treatment, insomnia, meningitis, mood swings, neuritis, neuropathy, paraparesis/paraplegia, paresthesia, personality changes, sensory disturbances, vertigo

Ophthalmic:Exophthalmos, glaucoma, increased intraocular pressure, posterior subcapsular cataracts, and central serous chorioretinopathy

Reproductive:Alteration in motility and number of spermatozoa

7 DRUG INTERACTIONS

Table 2: Drug Interactions with KHINDIVI
CYP3A4 Inhibitors
Clinical Impact: | Hydrocortisone is metabolized by cytochrome P450 3A4 (CYP3A4). Concomitant administration of inhibitors of CYP3A4 may lead to increases in serum concentrations of KHINDIVI and increase the risk of adverse reactions associated with the use of excessive doses.
Intervention: | Concomitant use of CYP3A4 inhibitors may require a decrease in the KHINDIVI dose.
Examples: | Anti-fungals:itraconazole, posaconazole, voriconazole Antibiotics:erythromycin and clarithromycin Antiretrovirals:ritonavir Grapefruit juice
CYP3A4 Inducers
Clinical Impact: | Hydrocortisone is metabolized by cytochrome P450 3A4 (CYP3A4). Concomitant administration of inducers of CYP3A4 may lead to decreases in serum concentrations of KHINDIVI and increase the risk of adverse reactions, including adrenal crisis.
Intervention: | Concomitant use of CYP3A4 inducers may require an increase in the KHINDIVI dose.
Examples: | Anticonvulsants: phenytoin, carbamazepine and oxcarbazepine Antibiotics: rifampicin and rifabutin Barbiturates:phenobarbital and primidone Antiretrovirals: efavirenz and nevirapine
Estrogen and Estrogen-Containing Products
Clinical Impact: | Oral estrogen and estrogen-containing oral contraceptives may interact with hydrocortisone by increasing serum cortisol-binding globulin (CBG) concentration. Concomitant use may reduce the efficacy of KHINDIVI by binding and delaying or preventing absorption.
Intervention: | Concomitant use of estrogen/estrogen containing products may require an increase in the KHINDIVI dose.
Antidiabetic Agents
Clinical Impact: | Corticosteroids in supraphysiologic doses may increase blood glucose concentrations.
Intervention: | Use of KHINDIVI in supraphysiologic doses may require a dose adjustment of antidiabetic agents.
Anticoagulant Agents
Clinical Impact: | Concomitant use of warfarin and corticosteroids usually results in inhibition of response to warfarin, although there have been some conflicting reports.
Intervention: | Monitor coagulation indices in patients receiving KHINDIVI and concomitant warfarin to maintain the desired anticoagulant effect.
Cyclosporine
Clinical Impact: | Increased activity of both cyclosporine and corticosteroids may occur when the two are used concurrently. Convulsions have been reported with concurrent use.
Intervention: | Monitor patients receiving KHINDIVI and concomitant cyclosporine.
Nonsteroidal Anti-inflammatory Drugs (NSAIDs)
Clinical Impact: | Concomitant use of NSAIDs and corticosteroids increases the risk of gastrointestinal adverse reactions. Aspirin should be used cautiously in conjunction with corticosteroids in hypoprothrombinemia. The clearance of salicylates may be increased with concurrent use of corticosteroids; this could lead to decreased salicylate serum levels or increase the risk of salicylate toxicity when corticosteroid is withdrawn.
Intervention: | Monitor patients receiving KHINDIVI and concomitant NSAIDs.

8 USE IN SPECIFIC POPULATIONS

8.1 Pregnancy

Risk Summary

Untreated adrenocortical insufficiency in pregnancy can result in a high rate of complications, including maternal mortality. The use of physiologic doses of hydrocortisone is not expected to cause major birth defects, miscarriage and adverse maternal and fetal outcomes. Available data from observational studies with hydrocortisone use in pregnancy have not identified a clear drug- associated risk of major birth defects, miscarriage or adverse maternal or fetal outcomes (see Data).

The estimated background risk of major birth defects and miscarriage for the indicated population is unknown. In the U.S. general population, the estimated background risk of major birth defects and miscarriage in clinically recognized pregnancies is 2–4% and 15–20%, respectively.

Data

Human Data

Available data from observational studies with hydrocortisone use in pregnant women have not identified a clear drug-associated risk of major birth defects, miscarriage or adverse maternal or fetal outcomes. Evidence from published epidemiologic studies suggest that there may be a small increased risk of cleft lip with or without cleft palate associated with first trimester systemic corticosteroid use in pregnant patients. However, the data are limited and report inconsistent findings, and studies have important methodological limitations, including non-randomized design, retrospective data collection, lack of dose-response data and the inability to control for confounders, such as underlying maternal disease and use of concomitant medications. In addition, unlike other corticosteroids, hydrocortisone is enzymatically deactivated by the placenta and therefore limits fetal exposure.

Animal Data

Corticosteroids have been shown to be teratogenic in many species when given in doses equivalent to the human dose. Animal studies in which corticosteroids have been given to pregnant mice, rats and rabbits without adrenocortical insufficiency have yielded an increased incidence of cleft palate in the offspring.

8.2 Lactation

Risk Summary

Cortisol is present in human milk. The use of hydrocortisone at a physiologic dose for adrenocortical insufficiency is not expected to adversely affect the breastfed infant or milk production. There are no data on the presence of hydrocortisone in breast milk, the effect on the breastfed infant or on milk production. The developmental and health benefits of breastfeeding should be considered along with the mother's clinical need for KHINDIVI and any potential adverse effects on the breastfed infant from KHINDIVI or from the underlying maternal condition.

8.4 Pediatric Use

The safety and effectiveness of KHINDIVI have been established in pediatric patients 5 years of age and older for replacement therapy of adrenocortical insufficiency and the information on this use is discussed throughout the labeling. Use of KHINDIVI for this indication is supported by findings of safety and efficacy in other approved hydrocortisone products, including supportive pharmacokinetic and safety data in pediatric patients with adrenocortical insufficiency.

KHINDIVI is not approved in pediatric patients less than 5 years of age. KHINDIVI contains the inactive ingredients polyethylene glycol 400, propylene glycol, and glycerin, which undergo substantial systemic absorption. These inactive ingredients, individually or in combination, may increase plasma osmolarity in all pediatric patients, especially in pediatric patients less than 5 years of age due to incomplete alcohol dehydrogenase maturity [see Warnings and Precautions (5.2)].

When prescribing KHINDIVI in pediatric patients 5 years of age and older, consider the combined daily amount of polyethylene glycol 400, propylene glycol, and glycerin from all sources including KHINDIVI and other drugs with inactive ingredients utilizing the same metabolic pathways as these inactive ingredients, which may increase exposure and lead to an increased risk of systemic toxicity [see Warnings and Precautions (5.2)] .

10 OVERDOSAGE

Treatment of acute overdosage is by supportive and symptomatic therapy.

11 DESCRIPTION

KHINDIVI contains hydrocortisone, a corticosteroid, also known as cortisol. The chemical name of hydrocortisone is 11β,17α,21-trihydroxy-pregn-4-ene-3,20-dione and it has the chemical formula of C21H30O5, and molecular weight of 362 g∙mol^–1. Hydrocortisone is a white or almost white powder soluble in the pH range of 1-7.

Structural formula of hydrocortisone:

KHINDIVI is a clear, colorless to slightly yellow colored viscous solution of hydrocortisone available for oral administration in a concentration of 1 mg/mL. The inactive ingredients are berry flavor, butylated hydroxyanisole, ethyl maltol, glycerin (623 mg/mL), methylparaben, propylparaben, polyethylene glycol 400 (500 mg/mL), propylene glycol (50 mg/mL), and sucralose.

12 CLINICAL PHARMACOLOGY

12.1 Mechanism of Action

Hydrocortisone is a glucocorticoid. Glucocorticoids, adrenocortical steroids, cause varied metabolic effects. In addition, they modify the body's immune responses to diverse stimuli.

12.2 Pharmacodynamics

Naturally occurring glucocorticoids (hydrocortisone and cortisone), which also have salt-retaining properties, are used as replacement therapy in adrenocortical deficiency states.

12.3 Pharmacokinetics

Absorption

Following oral administration of KHINDIVI (5 mg) in dexamethasone-suppressed healthy adult volunteers under fasted conditions, mean (range) maximum plasma concentration (Cmax) of hydrocortisone is 152 (98-210) ng/mL. Mean (range) time to reach maximum concentration (Tmax) is 0.5 (0.25-0.75) hours.

Effect of Food

No clinically significant differences in KHINDIVI pharmacokinetics were observed following administration of a high-fat meal.

Distribution

90% or more of circulating hydrocortisone is reversibly bound to protein.

The binding is accounted for by two protein fractions. One, corticosteroid-binding globulin is a glycoprotein; the other is albumin.

Following administration of 5 mg Hydrocortisone oral solution in dexamethasone-suppressed healthy adult volunteers under fasted conditions, mean (range) apparent (oral) volume of distribution (Vd/F) of hydrocortisone is 23 (5-59) L.

Elimination

Hydrocortisone is metabolized in the liver and most body tissues to hydrogenated and degraded forms such as tetrahydrocortisone and tetrahydrocortisol which are excreted in the urine, mainly conjugated as glucuronides, together with a very small proportion of unchanged hydrocortisone.

Following administration of 5 mg Hydrocortisone oral solution in dexamethasone-suppressed healthy adult volunteers under fasted conditions, mean (range) terminal half-life of hydrocortisone is about 0.95 (0.3-2.3) hours.

13 NONCLINICAL TOXICOLOGY

13.1 Carcinogenesis, Mutagenesis, Impairment of Fertility

No adequate studies in animals have been conducted with hydrocortisone to evaluate carcinogenic or mutagenic potential. Corticosteroids have been shown to impair fertility in male rats.

16 HOW SUPPLIED/STORAGE AND HANDLING

KHINDIVI is supplied as a colorless to slightly yellow colored, clear viscous solution:

Strength | Volume in Bottle | NDC
1 mg/mL | 473 mL | 71863-116-16

STORAGE AND HANDLING

Store at 2°C to 25°C (36°F to 77°F). Excursions permitted to 30°C (86°F) [see USP refrigerated and controlled room temperature]. Protect from light and heat.

Product must be used within 120 days of first opening. If not used within 120 days, the unused portion must be discarded.

17 PATIENT COUNSELING INFORMATION

Advise patients and/or caregivers to read the FDA-approved patient labeling (Medication Guide).

Administration Information

Instruct patients and/or caregivers to use an oral dosing syringe to correctly measure the prescribed amount of medication. Inform patients and/or caregivers that oral dosing syringes may be obtained from their pharmacy.

Advise patients and/or caregivers to take a sip of water immediately following administration to ensure all the solution has been swallowed.

For administration through a gastric tube, flush with 20 mL of water to ensure that the entire dose is delivered [see Dosage and Administration (2.2)].

Adrenal Crisis

Inform patients and/or caregivers that undertreatment or sudden discontinuation of KHINDIVI or switching to KHINDIVI from another oral hydrocortisone formulation, may lead to adrenocortical insufficiency, adrenal crisis, and death.

Inform patients and/or caregivers to switch to another oral hydrocortisone product and increase the dose during periods of stress, and not to use KHINDIVI for increased dosing during period of stress or acute events due to increased risk of systemic and gastrointestinal adverse reactions.

Inform the caregiver that potential dosing inaccuracy of the manipulated oral hydrocortisone formulation (e.g., split or crushed tablets, compounded formulations) may result in dosing differences when switching to KHINDIVI which may require dose adjustments. Advise caregivers to watch the patient for symptoms of adrenocortical insufficiency during the days after switching to KHINDIVI. Inform patient and/or caregiver to contact their healthcare provider if they have symptoms of adrenocortical insufficiency, prolonged vomiting, are severely ill or are unable to take oral medications [see Warnings and Precautions (5.1)] .

Systemic Adverse Reactions Due to Inactive Ingredients

Inform patients and/or caregivers that some inactive ingredients in KHINDIVI may increase the risk for hyperosmolarity, metabolic acidosis, loose stools, diarrhea, and other systemic adverse reactions, which may increase the risk of adrenal crisis. Patients and/or caregivers should contact the healthcare provider if patients have altered mental status, abnormal urine output, or are severely ill [see Warnings and Precautions (5.2)] .

Immunosuppression and Increased Risk of Infections

Advise patients and/or caregivers that greater than replacement dosage of corticosteroids can suppress the immune system and increase the risk of infections. Instruct patients and/or caregivers to contact their healthcare provider if they develop any infections [see Warnings and Precautions (5.3)] .

Growth Retardation

Discuss with caregivers that long-term use of corticosteroids in excessive doses may cause growth retardation in pediatric patients [see Warnings and Precautions (5.4)] .

Cushing's Syndrome

Inform patients and/or caregivers that prolonged use of corticosteroids in supraphysiologic doses may cause Cushing's syndrome and that symptoms and signs include weight gain, decreased height velocity, hyperglycemia, hypertension, edema, easy bruising, muscle weakness, red round face, depression, or mood swings [see Warnings and Precautions (5.5)].

Decrease in Bone Mineral Density

Inform patients and/or caregivers that corticosteroids decrease bone formation and increase bone resorption that may lead to osteoporosis [see Warnings and Precautions (5.6)] .

Psychiatric Adverse Reactions

Advise patients and/or caregivers that corticosteroid use may be associated with severe psychiatric adverse reactions such as euphoria, mania, psychosis with hallucinations or depression. Instruct caregivers and/or patients to seek medical advice if psychiatric symptoms develop [see Warnings and Precautions (5.7)] .

Ophthalmic Adverse Reactions

Inform patients and/or caregivers that ophthalmic effects such as cataract, glaucoma or central serous chorioretinopathy have been reported with prolonged use of high-dose corticosteroids. Instruct patients or caregivers to report any blurred vision or visual disturbances to their healthcare provider [see Warnings and Precautions (5.8)] .

Gastrointestinal Adverse Reactions

Discuss with patients and/or healthcare providers that use of corticosteroids may increase risk of gastrointestinal perforation in certain gastrointestinal disorders [see Warnings and Precautions (5.9)].

Risk of Kaposi's Sarcoma

Inform patients that they are at risk of developing Kaposi's sarcoma [see Warnings and Precautions (5.10)].

Vaccination

Inform patients and/or caregivers that administration of live vaccine may be acceptable [see Warnings and Precautions (5.11)].

KHINDIVI is manufactured for Eton Pharmaceuticals, Inc. by Tulex Pharmaceuticals, Inc., 5 Cedarbrook Dr., Cranbury, NJ 08512, USA.

KHINDIVI is covered by the following US patents: 11,904,046, and 12,133, 914.

PL-1-2.0

Medication Guide
KHINDIVI ™(kɪn-dɪv-i)
(hydrocortisone) oral solution

Read this Medication Guide before you start giving KHINDIVI to your child, and each time your child gets a refill. There may be new information. This information does not take the place of talking to your healthcare provider about your child's medical condition or treatment.

What is the most important information I should know about KHINDIVI?

KHINDIVI may cause serious side effects, including:

Adrenal gland problems. Not giving enough KHINDIVI, stopping KHINDIVI, or switching to KHINDIVI after taking another hydrocortisone medicine (the same class of medicines as KHINDIVI) by mouth, can cause serious and life-threatening adrenal gland problems including death. Do not stop giving KHINDIVI without talking to your healthcare provider. Tell your healthcare provider if your child has any of these symptoms:

- loss of appetite
- fatigue
- weakness

- joint pain
- nausea
- vomiting

- low blood sugar
- feeling lightheaded or dizzy
- problems with body salt (electrolyte) levels

Your healthcare provider will change the dose of KHINDIVI depending on your child's size. During episodes of acute infections, surgery, or major trauma, your healthcare provider may prescribe your child a different hydrocortisone medicine and increase the dose. If your child is vomiting, severely ill, or unable to take medicines by mouth, your healthcare provider may use corticosteroid medicines that are given directly into the bloodstream instead.

The amount of hydrocortisone in a dose of KHINDIVI may not be the same as in previous hydrocortisone medicines that your child takes by mouth if these oral hydrocortisone medicines have been changed (for example, crushed or compounded). When switching to KHINDIVI, your healthcare provider may need to prescribe a starting dose of KHINDIVI that is different from previous hydrocortisone medicines that your child may have been taking by mouth. Watch your child closely after being switched to KHINDIVI and contact your healthcare provider if your child has any symptoms of adrenal gland problems. Your healthcare provider may need to change the dose of KHINDIVI.

See " What are the possible side effects of KHINDIVI?" for more information about side effects.

What is KHINDIVI?

KHINDIVI is a prescription medicine that contains a medicine hydrocortisone. Hydrocortisone belongs to a group of medicines known as corticosteroids. Hydrocortisone is a synthetic version of the hormone cortisol. Cortisol is made naturally by the adrenal glands in the body. KHINDIVI (hydrocortisone) is a man-made (synthetic) corticosteroid used to replace the body's cortisol when the adrenal glands do not make enough (adrenal insufficiency) in children from 5 to 17 years of age.

Who should not take or be given KHINDIVI?

Do not give your child KHINDIVI if they:

- are allergic to hydrocortisone or any of the ingredients in KHINDIVI. See the end of this Medication Guide for a complete list of ingredients in KHINDIVI.
- have any reaction like swelling or shortness of breath after being given KHINDIVI. Get medical help right away and tell your healthcare provider as soon as possible as these can be signs of an allergic reaction.

What should I tell my healthcare provider before giving KHINDIVI?

Before you give your child KHINDIVI, tell your healthcare provider about all of your child's medical conditions, including if they:

- are feeling unwell, or their body is under stress because of surgery or trauma. Your healthcare provider may prescribe your child a different hydrocortisone medicine for a short period of time.
- have a fever or infection.
- have nausea, vomiting, or diarrhea.
- are due for vaccinations. Taking KHINDIVI should not stop your child from being vaccinated. Tell your healthcare provider when your child is due for vaccinations.
- are scheduled for surgery.
- cannot swallow medicines by mouth or are fed through a gastric tube.
- are pregnant or plan to become pregnant. It is not known if KHINDIVI will harm your child's unborn baby. Talk to your child's healthcare provider if your child is pregnant or plans to become pregnant.
- are breastfeeding or plan to breastfeed. It is not known if KHINDIVI passes into the breast milk. You and your child's healthcare provider should decide if your child will receive KHINDIVI while your child breastfeeds.

Tell your healthcare provider about all the medicines your child takes,including prescription and over-the-counter medicines, vitamins, and herbal supplements.

Some medicines, food and drink can affect the way that KHINDIVI works and may mean that your healthcare provider needs to change your child's dose of KHINDIVI.
Especially tell your healthcare provider if your child:

- takes medicines used to treat fungal infections such as itraconazole, posaconazole, and voriconazole.
- takes medicines used to treat bacterial infections such as rifampicin, rifabutin, erythromycin, and clarithromycin.
- takes medicines used to treat human immunodeficiency virus (HIV) infection and AIDS such as ritonavir, efavirenz, and nevirapine.
- takes seizure medicines such as phenytoin, carbamazepine, oxcarbazepine, phenobarbital, and primidone.
- takes estrogen.
- takes warfarin.
- takes nonsteroidal anti-inflammatory medicines such as aspirin and ibuprofen.
- takes cyclosporine.
- takes diabetes medicines.
- drinks grapefruit juice.

Know the medicines your child takes. Keep a list of them to show your healthcare provider and pharmacist when your child gets a new medicine.

How should I give KHINDIVI?

- Give KHINDIVI exactly as prescribed by your healthcare provider.
- Give KHINDIVI by mouth with or without food.
- Give a sip of water right away after giving KHINDIVI to make sure that all of the medicine has been swallowed.
- Give KHINDIVI using the oral syringe provided by the pharmacy.
- Do notstop giving KHINDIVI without talking to your healthcare provider. See " What is the most important information I should know about KHINDIVI?"
- KHINDIVI can be given through a gastric tube. After KHINDIVI is given through the gastric tube, flush the gastric tube with 20 mL of water right away to make sure all the medicine has been given.
- If your child takes too much KHINDIVI, call your healthcare provider right away or go to the nearest emergency room.

What are the possible side effects of KHINDIVI?

KHINDIVI may cause serious side effects, including:

- See " What is the most important information I should know about KHINDIVI?"
- Hyperosmolarity, metabolic acidosis, and stomach problems.Some of the ingredients in KHINDIVI may increase the risk for imbalance of salts and other substances in your blood leading to fluid shifts (hyperosmolarity), too much acid in the blood (metabolic acidosis), vomiting, loose stools, diarrhea, and other side effects, which may increase the risk of adrenal gland problems. Tell your healthcare provider if your child has confusion (altered mental status), urine output that is not normal, or is severely ill. Your healthcare provider may prescribe your child a different hydrocortisone medicine.
- Weakened immune system and increased risk of infections.Taking too much KHINDIVI can weaken your body's immune system and increase your chance of getting infections. Tell your healthcare provider if your child develops any infections or has any of these symptoms:

- fever
- cough
- flu-like symptoms

- stomach area (abdominal) pain
- diarrhea

- Slowed growth in children. Taking too much KHINDIVI and taking it for long periods of time can affect your child's growth. Tell your healthcare provider if you are worried about your child's growth. Your healthcare provider will change the dose depending on your child's size.
- Cushing's syndrome.Taking too much KHINDIVI and taking it for long periods of time can cause Cushing's syndrome. Tell your healthcare provider if your child has any of these symptoms:

- weight gain
- slowed growth in height

- high blood sugar
- high blood pressure

- swelling
- bruising easily

- muscle weakness
- red, round face

- feeling depressed
- mood swings

- Weak, brittle, or soft bones.KHINDIVI can affect your child's bones. Your healthcare provider will change the dose depending on your child's size and will monitor your child's growth and bones.
- Changes in behavior.Your child's behavior may change after starting or during treatment with KHINDIVI. Tell your healthcare provider right away if your child develops any changes in behavior including:
  - strong feelings of happiness and excitement.
  - overexcited and overactive.
  - loss of contact with reality, with feelings that are not real, and mental confusion.
  - depression.
- Vision problems.Tell your healthcare provider if your child develops blurred vision or other vision problems during treatment with KHINDIVI. Your healthcare provider may have your child see an eye doctor.
- Gastrointestinal problems.KHINDIVI can affect your child's stomach or intestine. Tell your healthcare provider if your child has gastrointestinal illnesses such as stomach or intestinal ulcers, infections, or gastrointestinal surgery.
- Risk of Kaposi's Sarcoma if your child takes too much KHINDIVI.Kaposi's Sarcoma has happened in people who receive corticosteroid therapy, most often for treatment of long-lasting (chronic) conditions. Taking too much KHINDIVI over a long period of time can increase your child's risk of developing Kaposi's Sarcoma.
- Vaccinations.Administration of live vaccine may be acceptable while taking KHINDIVI.

The most common side effects of KHINDIVI include:

- fluid retention
- behavioral and mood changes

- change in blood sugar (glucose) tolerance
- increased appetite and weight gain

- increase in blood pressure

These are not all the possible side effects of KHINDIVI.
Call your doctor for medical advice about side effects. You may report side effects to FDA at 1-800-FDA-1088.

How should I store KHINDIVI?

- Store KHINDIVI in the refrigerator between 36°F to 46°F (2°C to 8°C) or at room temperature between 68°F to 77°F (20°C to 25°C).
- Protect from light and heat.
- After the bottle has been opened, use KHINDIVI within 120 days. Throw away any KHINDIVI that has not been used within 120 days after the bottle has been opened.

Keep KHINDIVI and all medicines out of the reach of children.

General information about the safe and effective use of KHINDIVI.

Medicines are sometimes prescribed for purposes other than those listed in a Medication Guide. Do not use KHINDIVI for a condition for which it was not prescribed. Do not give KHINDIVI to other people, even if they have the same symptoms that you have. It may harm them. You can ask your pharmacist or healthcare provider for information about KHINDIVI that is written for health professionals.

What are the ingredients in KHINDIVI?

Active ingredient:hydrocortisone

Inactive ingredients: berry flavor, butylated hydroxyanisole, ethyl maltol, glycerin, methylparaben, propylparaben, polyethylene glycol, propylene glycol, and sucralose.

KHINDIVI is manufactured for Eton Pharmaceuticals, Inc. by Tulex Pharmaceuticals, Inc., 5 Cedarbrook Dr., Cranbury, NJ 08512, USA.
KHINDIVI is covered by the following US patent: 11,904,046.
For more information, go to www.KHINDIVI.com or call 1-833-343-2500.

This Medication Guide has been approved by the U.S. Food and Drug Administration.

Issued: 06/2025

PL-2-2.0

PRINCIPAL DISPLAY PANEL - 473 mL Bottle Label

NDC-71863-116-16
Rx Only

Khindivi
(hydrocortisone)
oral solution

1 mg/mL

For Oral Use Only

ATTENTION PHARMACIST:
Dispense the following to each patient:

- Accompanying Medication Guide
- Oral Dosing Syringe

16 oz (473 mL)

Manufactured for:
eTon
PHARMACEUTICALS
Deer Park, IL 60010, USA

LAB-1613-v3
Rev. 05/2025